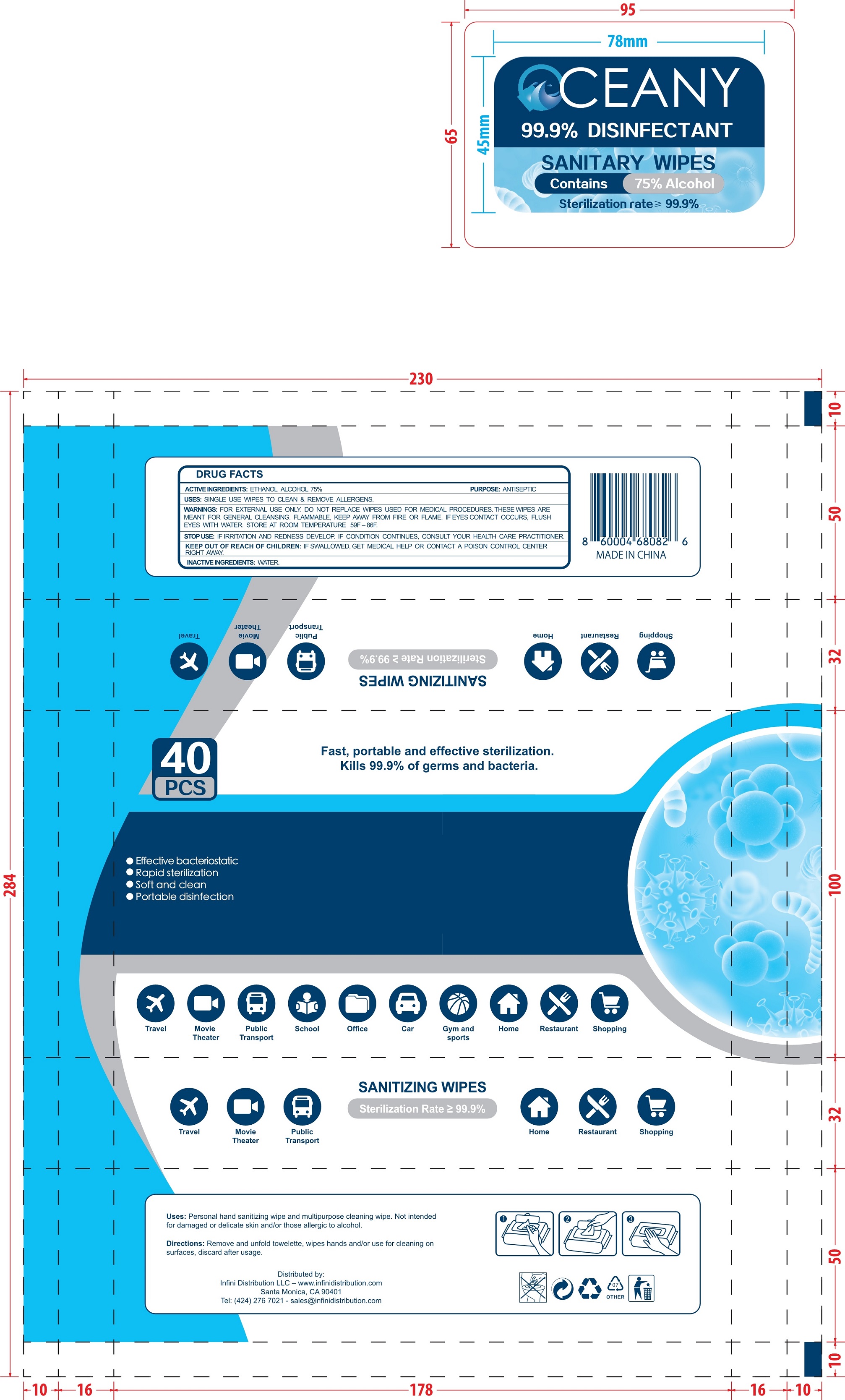 DRUG LABEL: SANITIZING WIPES
NDC: 41382-008 | Form: CLOTH
Manufacturer: Jinhua Dubei Maternal & Infant Products Co., Ltd.
Category: otc | Type: HUMAN OTC DRUG LABEL
Date: 20200805

ACTIVE INGREDIENTS: ALCOHOL 75 mL/100 1
INACTIVE INGREDIENTS: WATER

41382-008 SANITIZING WIPES

Active Ingredient(s)

Alcohol 75% v/v. Purpose: Antiseptic

Purpose

ANTISEPTIC.

Use

- Personal hand sanitizing wipe and multipurpose cleaning wipe.Not intended for damaged or delicate skin and/or those allergic to alcohol.
- Single use wipes to clean & remove allergens.

Warnings

- FOR EXTERNAL USE ONLY.
- DO NOT REPLACE WIPES USED FOR MEDICAL PROCEDURES.
- THESE WIPES ARE MEANT FOR GENERAL CLEANSING.
  - FLAMMABLE , KEEP AWAY FROM OR FLAME.
  - IF EYES CONTACT OCCURS,FLUSH EYES WITH WATER.
  - STORE AT ROOM TEMPERATURE 59F-86F.

Do not use

- in children less than 2 months of age
- on open skin wounds

When using this product keep out of eyes, ears, and mouth. In case of contact with eyes, rinse eyes thoroughly with water.
Stop use and ask a doctor if irritation or rash occurs. These may be signs of a serious condition.
Keep out of reach of children. If swallowed, get medical help or contact a Poison Control Center right away.

STOP USE :IF IRRITATION AND REDNESS DEVELOP. IF CONDITION COTINUES, CONSULT YOUR HEALTH CARE PRACTITIONER.

Keep out of reach of children. If swallowed, get medical help or contact a Poison Control Center right away.

Directions

- Place enough product on hands to cover all surfaces. Rub hands together until dry.
- Supervise children under 6 years of age when using this product to avoid swallowing.

Other information

- Store between 15-30C (59-86F)
- Avoid freezing and excessive heat above 40C (104F)

Inactive ingredients

purified water USP

Package Label - Principal Display Panel

40 cloth in 1 bag ndc:41382-008-01